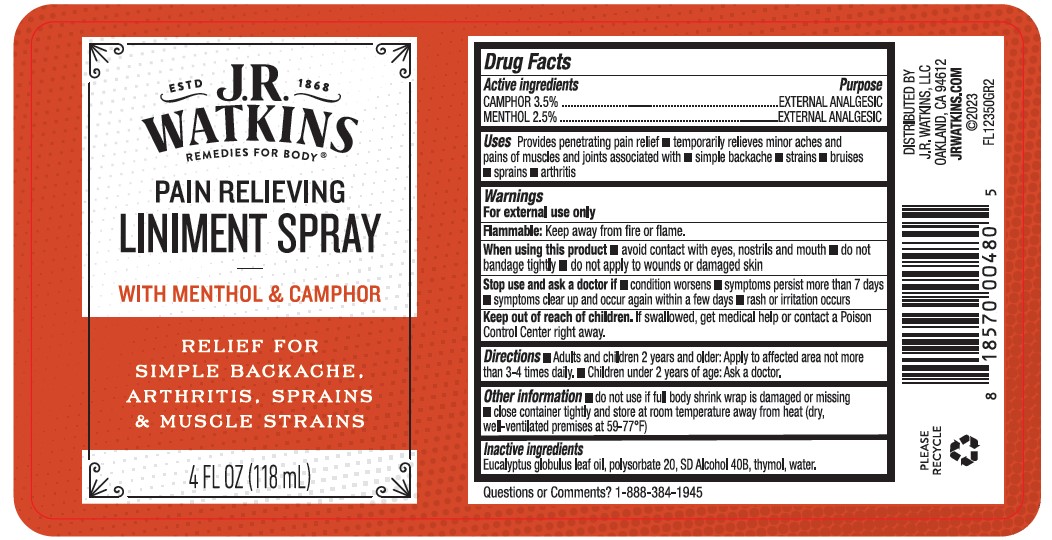 DRUG LABEL: Pain Relieving Liniment
NDC: 72342-050 | Form: SPRAY
Manufacturer: J.R. Watkins, LLC.
Category: otc | Type: HUMAN OTC DRUG LABEL
Date: 20240402

ACTIVE INGREDIENTS: CAMPHOR (NATURAL) 3.5 g/100 mL; MENTHOL, UNSPECIFIED FORM 2.5 g/100 mL
INACTIVE INGREDIENTS: ALCOHOL; WATER; THYMOL; EUCALYPTUS OIL; POLYSORBATE 20

Pain Relieving Liniment Spray

Drug Facts

ACTIVE INGREDIENT

Active ingredients | Purpose
CAMPHOR 3.5% | EXTERNAL ANALGESIC
MENTHOL 2.5% | EXTERNAL ANALGESIC

Uses

Provides penetrating pain relief

temporarily relieves minor aches and pains of muscles and joints associated with

- simple backache
- strains
- bruises
- sprains
- arthritis

Warnings

For external use only

Flammable:Keep away from fire or flame.

When using this product

- avoid contact with eyes, nostrils and mouth
- do not bandage tightly
- do not apply to wounds or damaged skin

Stop use and ask a doctor if

- condition worsens
- symptoms persist for more than 7 days
- symptoms clear up and occur again within a few days
- rash or irritation occurs

Keep out of reach of children.If swallowed, get medical help or contact a Poison Control Center right away.

Directions

- Adults and children 2 years and older: Apply to affected area not more than 3-4 times daily.
- Children under 2 years of age: Ask a doctor.

Other information

- do not use if full body shrink wrap is damaged or missing
- close container tightly and store at room temperature away from heat (dry, well-ventilated premises at 59-77°F)

Inactive ingredients

Eucalyptus globulus leaf oil, polysorbate 20, SD Alcohol 40B, thymol, water.

Questions or Comments?

1-800-243-9423

RECENT MAJOR CHANGES

Uses [Indications and Usage Section]

- Added "Provides penetrating pain relifef" at the beginning of the section - change incorporated in 3/2024

PRINCIPAL DISPLAY PANEL - 118 mL Bottle Box

ESTD J.R. 1868

WATKINS

REMEDIES FOR BODY®

PAIN RELIEVING
LINIMENT SPRAY

WITH MENTHOL & CAMPHOR

RELIEF FOR
SIMPLE BACKACHE,
ARTHRITIS, SPRAINS
& MUSCLE STRAINS

4 FL OZ (118 mL)